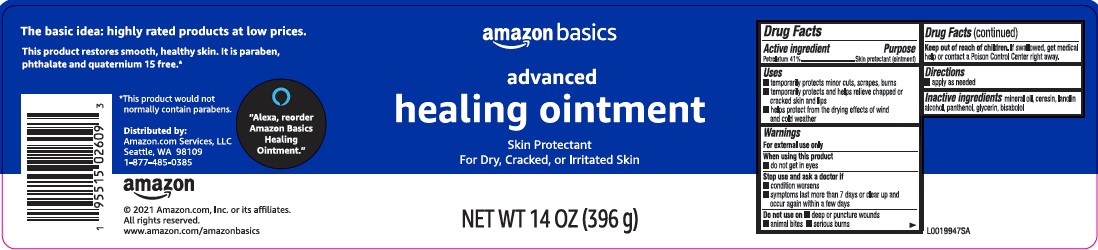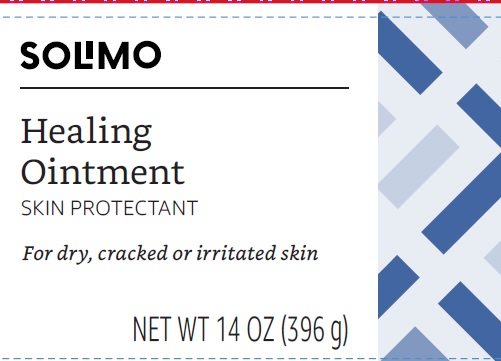 DRUG LABEL: Advanced Healing
NDC: 72288-247 | Form: OINTMENT
Manufacturer: Amazon.Com Services LLC
Category: otc | Type: HUMAN OTC DRUG LABEL
Date: 20250627

ACTIVE INGREDIENTS: PETROLATUM 410 mg/1 g
INACTIVE INGREDIENTS: MINERAL OIL; CERESIN; LANOLIN ALCOHOLS; PANTHENOL; GLYCERIN; LEVOMENOL

Basics_Solimo 247.000/247AA-AC
Healing Ointment for Dry and Cracked Skin

Active ingredient

Petrolatum 41%

Purpose

Skin protectant (ointment)

Uses

- temporarily protects minor cuts, scrapes, burns
- temporarily protects and helps relieve chapped and cracked skin and lips
- helps protect from the drying effects of wind and cold weather

Warnings

For external use only

When using this product

- do not get in eyes

Stop use and ask a doctor if

- condition worsens
- symptoms last more than 7 days or clear up and occur again within a few days

Do not use on

- deep or puncture wounds
- animal bites
- serious burns

Keep out of reach of children.

If swallowed get medical help or contract a Poison Control Center right away.

Directions

- apply as needed

Inactive ingredients

mineral oil, ceresin, lanolin alcohol, panthenol, glycerin, bisabolol

ADVERSE REACTION

The basic idea: highly rated products at low prices.

This product restores smooth, healthy skin. It is paraben, phthalate and quaternium 15 free.*

*This product would not normally contain parabens.

DISTRIBUTED BY:

Amazon.com Services, LLC

Seattle, WA 98109

1-877-485-0385

amazon

©2021 Amazon.com, Inc. or its afiliates.

All rights reserved.

www.amazon.com/amazonbasics

"Alexa, reorder Amazon Basics Healing Ointment."

principal display panel

SOLIMO

Healing Ointment

SKIN PROTECTANT

For dry, cracked or irritated skin

NET WT 14 OZ (396 g)

principal display panel

amazon basics

advanced

healing ointment

Skin Protectant

For Dry, Cracked, or Irritated Skin

NET WT 14 OZ (396 g)